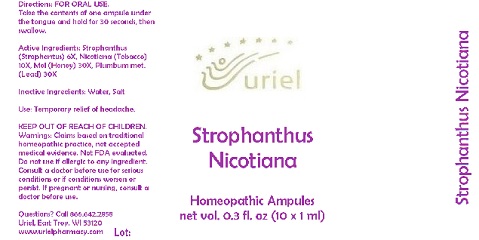 DRUG LABEL: Strophanthus Nicotiana
NDC: 48951-8218 | Form: LIQUID
Manufacturer: Uriel Pharmacy Inc.
Category: homeopathic | Type: HUMAN OTC DRUG LABEL
Date: 20180524

ACTIVE INGREDIENTS: STROPHANTHUS HISPIDUS SEED 6 [hp_X]/1 mL; TOBACCO LEAF 10 [hp_X]/1 mL; HONEY 30 [hp_X]/1 mL; LEAD 30 [hp_X]/1 mL
INACTIVE INGREDIENTS: WATER; SODIUM CHLORIDE

Strophanthus Nicotiana

INDICATIONS AND USAGE

Directions: FOR ORAL USE.

DOSAGE AND ADMINISTRATION

Take the contents of one ampule under the tongue and hold for 30 seconds, then swallow.

ACTIVE INGREDIENT

Active Ingredients: Strophanthus e sem. 6X, Nicotiana e fol. 10X, Mel 30X, Plumbum metallicum 30X

Inactive Ingredients: Water, Salt

PURPOSE

Use: Temporary relief of headache.

KEEP OUT OF REACH OF CHILDREN.

WARNINGS

Warnings: Claims based on traditional homeopathic practice, not accepted medical evidence. Not FDA evaluated. Do not use if allergic to any ingredient. Consult a doctor before use for serious conditions or if conditions worsen or persist. If pregnant or nursing, consult a doctor before use.

QUESTIONS

Questions? Call 866.642.2858 Uriel, East Troy, WI 53120 www.urielpharmacy.com